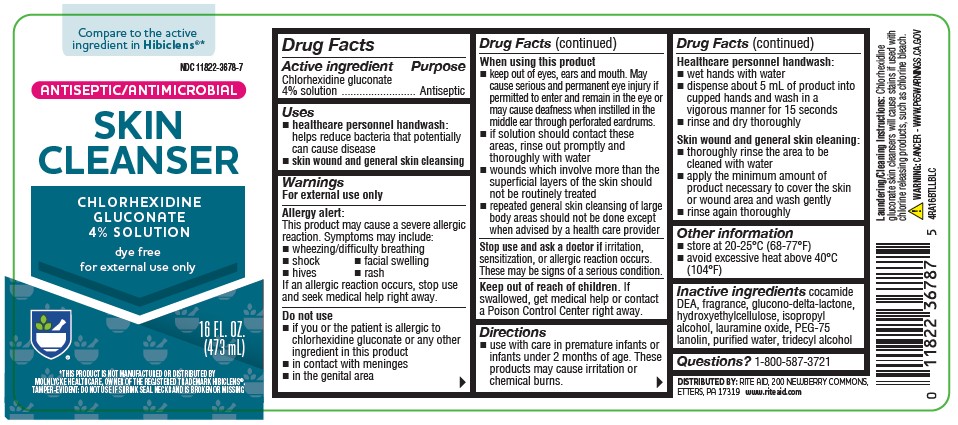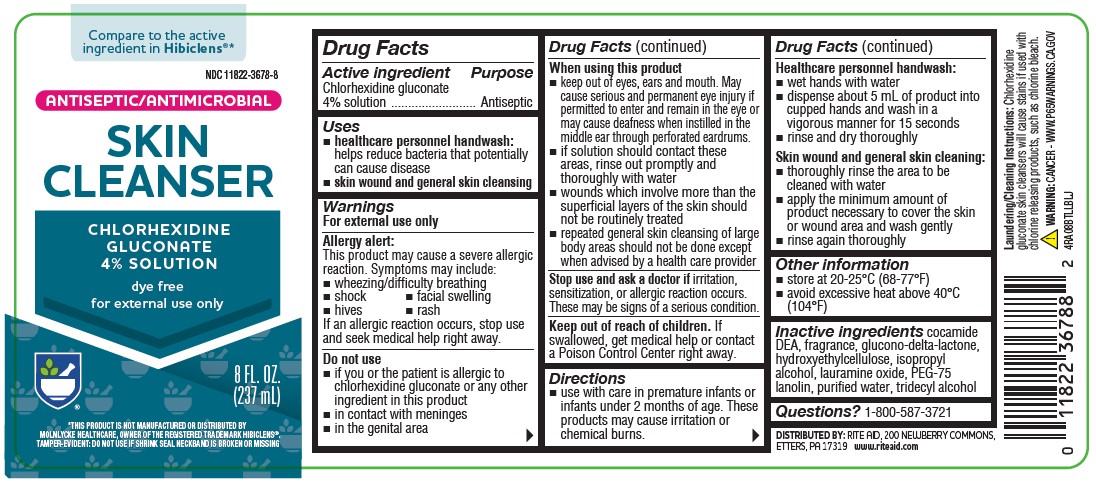 DRUG LABEL: Antiseptic Skin Cleanser
NDC: 11822-3678 | Form: LIQUID
Manufacturer: Rite Aid Corporation
Category: otc | Type: HUMAN OTC DRUG LABEL
Date: 20231106

ACTIVE INGREDIENTS: CHLORHEXIDINE GLUCONATE 4 mg/100 mL
INACTIVE INGREDIENTS: GLUCONOLACTONE; LAURAMINE OXIDE; COCO DIETHANOLAMIDE; PEG-75 LANOLIN; HYDROXYETHYL CELLULOSE (2000 CPS AT 1%); ISOPROPYL ALCOHOL; WATER; TRIDECYL ALCOHOL

4% Rite Aid 8/16oz

Active Ingredients

Chlorhexidine Gluconate 4% Solution

Purpose

Antiseptic

Uses

- healthcare personnel handwash: helps reduce bacteria that potentially can cause disease
- skin wound and general skin cleansing

Warnings

For external use only

Allergy alert: This product may cause severe allergic reaction. Symptoms may include:

- wheezing/difficulty breathing
- shock
- facial swelling
- hives
- rash

If an allergc reaction occurs, stop use and seek medical help right away.

Do not use

- if you or the patient is allergic to chlorhexidine gluconate or any other ingredient in this product
- in contact with meninges
- in the genital area

Keep out of reach of children

If swallowed, get medical help or contact a Poison Control Center right away.

Stop use and ask a doctor if

irritation, sensitization, or allergic reaction occurs. These may be signs of a serious condition.

When using this product

- keep out of eyes, ears, and mouth. May cause serious and permanent eye injury if permitted to enter and remain in the eye or may cause deafness when instilled in the middle ear through perforated eardurms.
- if solution should contact these areas, rinse out promptly and thoroughly with water
- wounds which involve more than the superficial layers of the skin should not be routinely treated
- repeated general skin cleansing of large body areas should not be done except when advised by a health care provider

Directions

- use with care in premature infants or infants under 2 months of age. These products may cause irritation or chemical burns.

Healthcare personnel handwash:

- wet hands with water
- dispense about 5 mL of product into cupped hands and wash in a vigorous manner for about 15 seconds
- rinse and dry thoroughly
- repeat procedure for an additional 2 minutes and dry with a sterile towel

Skin wound and normal skin cleansing:

- thoroughly rinse the area to be cleaned with water
- apply the minimum amount of product necessary to cover the skin or wound area and wash gently
- rinse again thoroughly

Other information

- store at 20-25°C (68-77°F)
- avoid excessive heat above 40°C (104°F)

Inactive ingredients

cocamide DEA, fragrance, glucono-delta-lactone, hydroxyethylcellulose, isopropyl alcohol, lauramine oxide, PEG-75 lanolin, purified water, tridecyl alcohol.

Questions or comments?

1-800-587-3721

OTHER SAFETY INFORMATION

Laundering/Cleaning Instructions: Chlorhexidine gluconate skin cleansers will cause stains if used with chlorine releasing products, such as bleach.

WARNING: Cancer - www.P65Warnings.ca.gov

*This product is not manufactured or distributed by Mölnlycke Healthcare, owner of the registered trademark Hibiclens®.

TAMPER-EVIDENT: Don't not use if shrink seal neackband is broken or missing.

DISTRIBUTED BY: RITE AID,

200 Newberry Commons, Etter, PA 17319

www.riteaid.com

IF YOU'RE NOT SATISFIED, WE'LL HAPPILY REFUND YOUR MONEY.

4RA08BTLLBLJ

Active ingredient

Chlorhexidine gluconate 4% solution

Purpose

Antiseptic

Uses

- healthcare personnel handwash: helps reduce bacteria that potentially can cause disease
- skin wound and general skin cleansing

Warnings

For external use only

Allergy alert:

This product may cause a severe allergic reaction. Symptoms may include:

- wheezing/difficulty breathing
- shock
- facial swelling
- hives
- rash

If an allergic reaction occurs, stop use and seek medical help right away.

Do not use

- if you or the patient is allergic to chlorhexidine gluconate or any other ingredient in this product
- in contact with the meninges
- in the genital area

When using this product

- keep out of eyes, ears, and mouth. May cause serious and permanent eye injury if permitted to enter and remain in the eye or may cause deafness when instilled in the middle ear through perforated eardrums.
- if solution should contact these areas, rinse out promptly and thoroughly with water
- wounds which involve more than the superficial layers of the skin should not be routinely treated
- repeated general skin cleansing of large body areas should not be done except when advised by a health care provider

Stop use and ask a doctor if

irritation, sensitization, or allergic reaction occurs. These may be signs of a serious condition.

Keep out of reach of children

If swallowed, get medical help or contact Poison Control Center right away.

Directions

- use with care in premature infants or infants under 2 months of age. These products may cause irritation or chemical burns.

Healthcare personnel handwash:

- wet hands with water
- dispense about 5 mL of product into cupped hands and wash in a vigorous manner for about 15 seconds
- rinse and dry thoroughly

Skin wound and general skin cleansing:

- thoroughly rinses the area to be cleaned with water
- apply the minimum amount of product necessary to cover the skin or wound area and wash gently
- rinse again thoroughly

Other information

- store at 20-25°C (68-77°F)
- avoid excessive heat above 40°C (104°F)

Inactive ingredient

cocmide DEA, fragrance, glucono-delta-lactone, hydroxyethylcellulose, isopropyl alcohol, lauramine oxide, PEG-75 lanolin, purified water, tridecyl alcohol.

Questions or comments?

1-800-587-3721

OTHER SAFETY INFORMATION

Laundering/Cleaning Instructions: Chlorhexidine gluconate skin cleansers will cause stains if used with chlorine releasing products, such as bleach.

WARNING: Cancer - www.P65Warnings.ca.gov

*This product is not manufactured or distributed by Mölnlycke Healthcare, owner of the registered trademark Hibiclens®.

TAMPER-EVIDENT: Don't not use if shrink seal neackband is broken or missing.

DISTRIBUTED BY: RITE AID,

200 Newberry Commons, Etter, PA 17319

www.riteaid.com

IF YOU'RE NOT SATISFIED, WE'LL HAPPILY REFUND YOUR MONEY.

4RA16BTLLBLC

Uses

Dosage and Administration

Uses: removal of surgical handscrub (11/23)

Direction: removal of surgical handscurb (11/23)

Package label and principal display panel

Compare to the active ingredient in Hibiclens®*

NDC 11822-3678-8

ANTISEPTIC/ANTIMICROBIAL

SKIN CLEANSER

CHLORHEXIDINE GLUCONATE

4% SOLUTION

dye free

for external use only

TAMPER-EVIDENT: DO NOT USE IF SHRINK SEAL NECKBAND IS BROKEN OR MISSING

8 FL OZ (237mL)

Principal display panel

Compare to the active ingredient in Hibiclens®*

NDC 11822-3678-7

ANTISEPTIC/ANTIMICROBIAL

SKIN CLEANSER

CHLORHEXIDINE GLUCONATE

4% SOLUTION

dye free

for external use only

TAMPER-EVIDENT: DO NOT USE IF SHRINK SEAL NECKBAND IS BROKEN OR MISSING

16 FL OZ (473 mL)